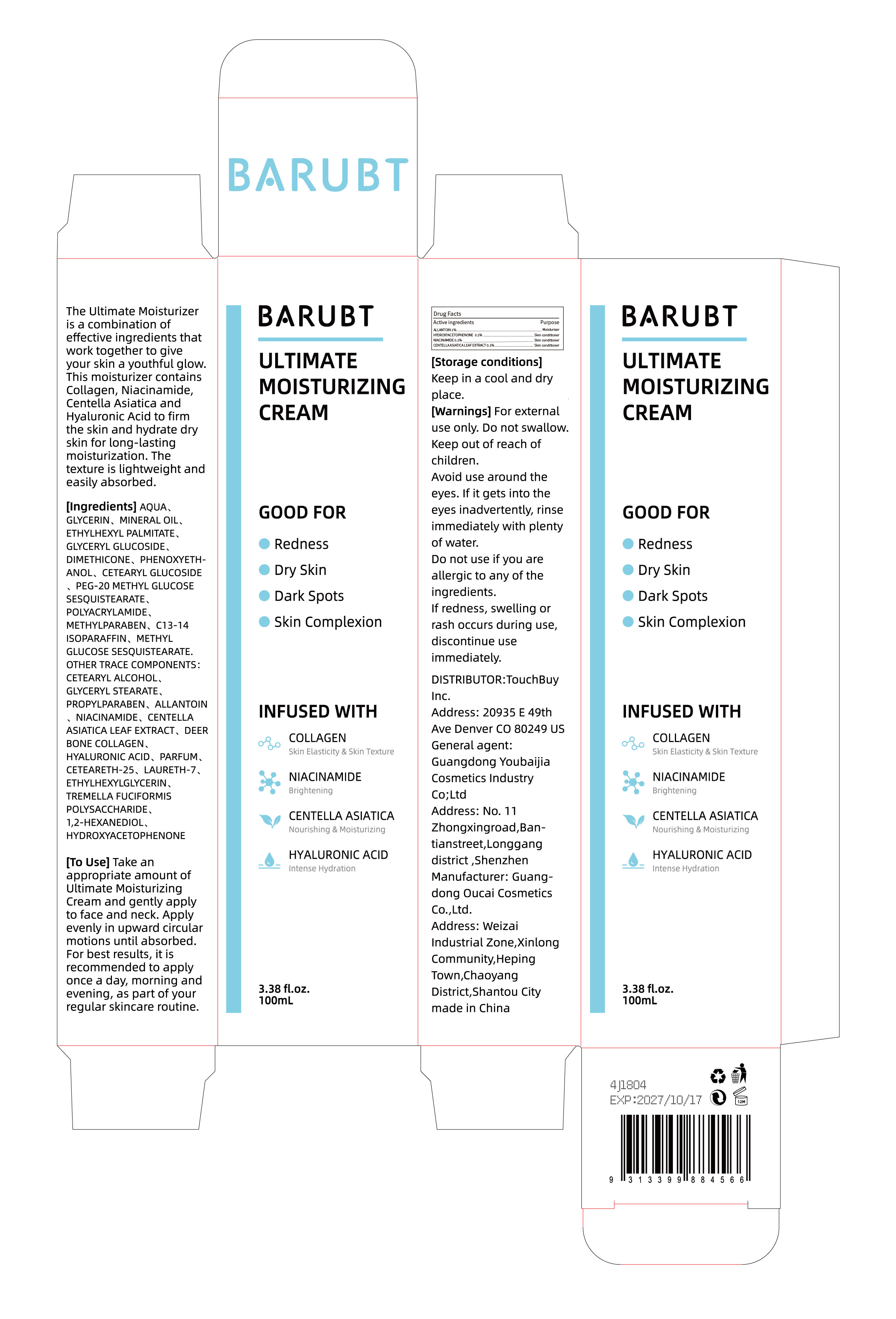 DRUG LABEL: BARUBT Ultimate Moisturizing Cream
NDC: 84712-036 | Form: CREAM
Manufacturer: Guangdong Youbaijia Cosmetic Industry Co., Ltd
Category: otc | Type: HUMAN OTC DRUG LABEL
Date: 20241127

ACTIVE INGREDIENTS: CENTELLA ASIATICA LEAF 0.1 g/100 mL; NIACINAMIDE 0.1 g/100 mL; HYDROXYACETOPHENONE 0.1 g/100 mL; ALLANTOIN 1 g/100 mL
INACTIVE INGREDIENTS: MINERAL OIL 5 g/100 mL

ACTIVE INGREDIENT

ALLANTOIN 1%
HYDROXYACETOPHENONE 0.1%
NIACINAMIDE 0.1%
CENTELLA ASIATICA LEAF EXTRACT 0.1%

INACTIVE INGREDIENT

AQUA. GLYCERIN, MINERAL OIL. ETHYLHEXYL PALMITATE, GLYCERYL GLUCOSIDE. DIMETHICONE, PHENOXYETH- ANOL, CETEARYL GLUCOSIDE PEG-20 METHYL GLUCOSE SESQUISTEARATE, POLYACRYLAMIDE, METHYLPARABEN, C13-14 ISOPARAFFIN, METHYL GLUCOSE SESQUISTEARATE. OTHER TRACE COMPONENTS : CETEARYL ALCOHOL, GLYCERYL STEARATE, PROPYLPARABEN, DEER BONE COLLAGEN. HYALURONIC ACID, PARFUM, CETEARETH-25, LAURETH-7, ETHYLHEXYLGLYCERIN, TREMELLA FUCIFORMIS POLYSACCHARIDE, 1,2-HEXANEDIOL

DO NOT USE

on damaged or broken skin

Keep away from children. Do not swallow.

PURPOSE

effective ingredients that work together to give your skin a youthful glow.

QUESTIONS

Contact name: Jessie Peng
Company phone number: +1 818 579 7288
Company e-mail: jessie@registeragentllc.com

STOP USE

lf skin becomes red or irritated, discontinue use immediately and wash with water.

WHEN USING

keep out of eyes. Rinse with water to remove.

INDICATIONS AND USAGE

The Ultimate Moisturizer is a combination of effective ingredients that work together to give your skin a youthful glow.This moisturizer contains Collagen, Niacinamide,Centella Asiatica and Hyaluronic Acid to firm the skin and hydrate dry skin for long-lasting moisturization. The texture is lightweight and easily absorbed.

DOSAGE AND ADMINISTRATION

Take an appropriate amount of Ultimate Moisturizing Cream and gently apply to face and neck. Apply evenly in upward circular motions until absorbed.For best results, it is recommended to apply once a day, morning and evening, as part of your regular skincare routine.

STORAGE AND HANDLING

Keep away from light and in a dry place.

WARNINGS

For external use only.